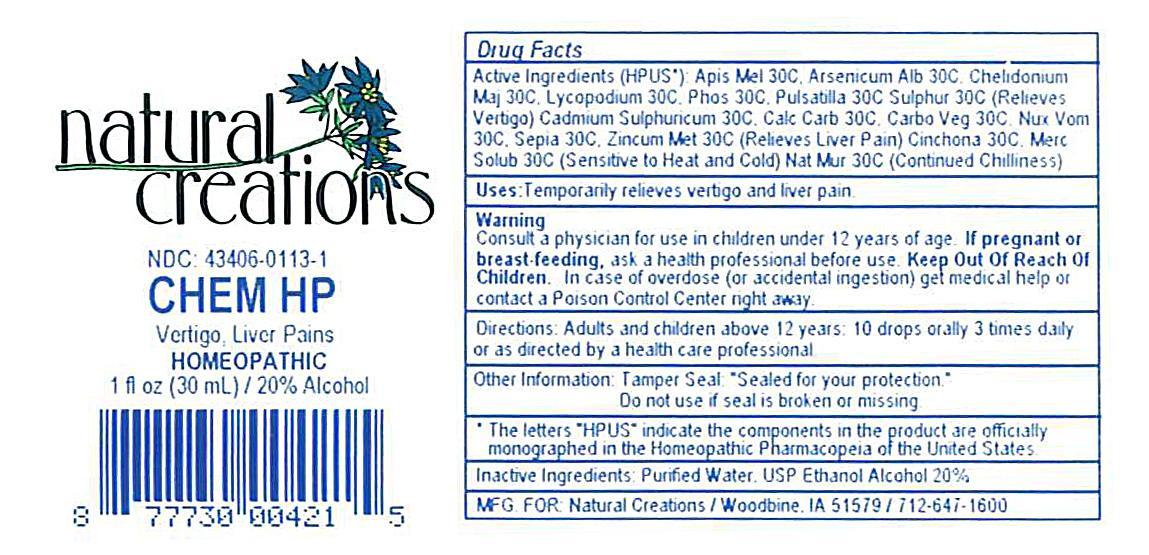 DRUG LABEL: CHEM HP
NDC: 43406-0113 | Form: LIQUID
Manufacturer: Natural Creations, Inc.
Category: homeopathic | Type: HUMAN OTC DRUG LABEL
Date: 20121011

ACTIVE INGREDIENTS: APIS MELLIFERA 30 [hp_C]/1 mL; ARSENIC TRIOXIDE 30 [hp_C]/1 mL; CADMIUM SULFATE 30 [hp_C]/1 mL; OYSTER SHELL CALCIUM CARBONATE, CRUDE 30 [hp_C]/1 mL; ACTIVATED CHARCOAL 30 [hp_C]/1 mL; CHELIDONIUM MAJUS 30 [hp_C]/1 mL; CINCHONA OFFICINALIS BARK 30 [hp_C]/1 mL; LYCOPODIUM CLAVATUM SPORE 30 [hp_C]/1 mL; MERCURIUS SOLUBILIS 30 [hp_C]/1 mL; SODIUM CHLORIDE 30 [hp_C]/1 mL; STRYCHNOS NUX-VOMICA SEED 30 [hp_C]/1 mL; PHOSPHORUS 30 [hp_C]/1 mL; PULSATILLA VULGARIS 30 [hp_C]/1 mL; SEPIA OFFICINALIS JUICE 30 [hp_C]/1 mL; SULFUR 30 [hp_C]/1 mL; ZINC 30 [hp_C]/1 mL
INACTIVE INGREDIENTS: WATER; ALCOHOL

CHEM HP

ACTIVE INGREDIENT

ACTIVE INGREDIENTS (HPUS*): Apis Mellifica 30C, Arsenicum Album 30C, Cadmium Sulphuricum 30C, Calcarea Carbonica 30C, Carbo Vegetabilis 30C, Chelidonium Majus 30C, China Officinalis 30C, Lycopodium Clavatum 30C, Mercurius Solubilis 30C, Natrum Muriaticum 30C, Nux Vomica 30C, Phosphorus 30C, Pulsatilla 30C, Sepia Succus 30C, Sulfur 30C, Zincum Metallicum 30C

INDICATIONS AND USAGE

Uses: Temporarily relieves vertigo and liver pain.

PURPOSE

USES: Temporarily relieves vertigo and liver pain.

KEEP OUT OF REACH OF CHILDREN

KEEP OUT OF THE REACH OF CHILDREN. In case of overdose (or accidental ingestion) get medical help or contact a Poison Control Center.

WARNING:

Consult a physician for use in children under 12 years of age. IF PREGNANT OR BREAST-FEEDING, ask a health care professional before use. KEEP OUR OF THE REACH OF CHILDREN. In case of overdose (or accidental ingestion) get medical help or contact a Poison Control Center right away.

DOSAGE AND ADMINISTRATION

DIRECTIONS: Adults and children above 12 years: 10 drops orally 3 times daily, or as directed by a health care professional.

OTHER INFORMATION: Tamper Seal: "Sealed for your protection." Do not use if seal is broken or missing.

REFERENCES

*The letters "HPUS" indicate the components in the product are officially monographed in the Homeopathic Pharmacopeia of the United States.

INACTIVE INGREDIENTS: Purified Water, USP Ethanol Alcohol 20%

QUESTIONS

QUESTION AND COMMENTS?

MFG FOR: Natural Creations / Woodbine, IA / 51579 712.647.1600

LOT:

PACKAGE LABEL

NDC: 43406-0113-1

CHEM HP

Vertigo, Liver Pains

HOMEOPATHIC

1 fl oz (30 mL) / 20% Alcohol

UPC: 877730004215